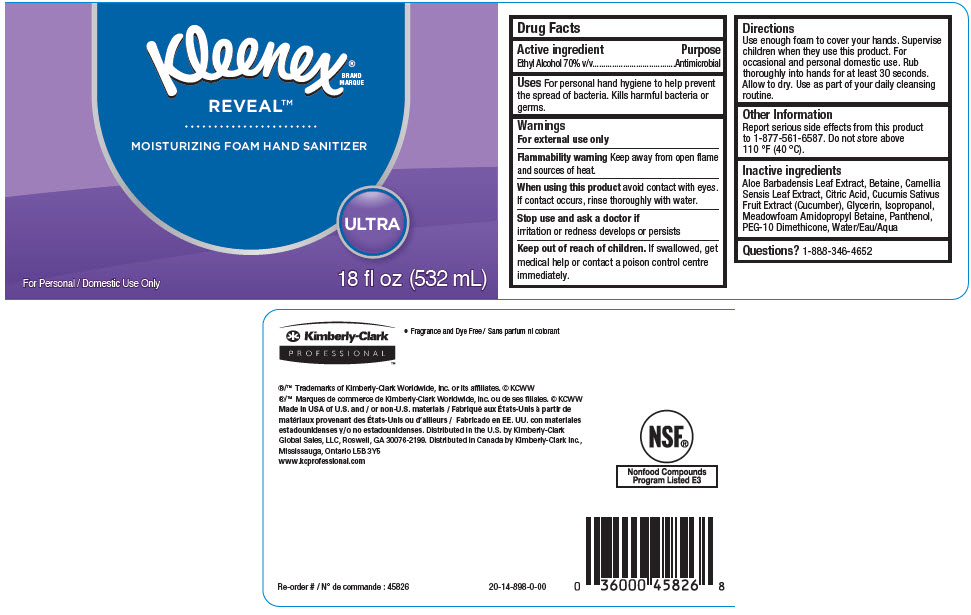 DRUG LABEL: Kleenex Reveal Moisturizing Foam Hand Sanitizer
NDC: 55118-531 | Form: SOLUTION
Manufacturer: Kimberly-Clark
Category: otc | Type: HUMAN OTC DRUG LABEL
Date: 20241211

ACTIVE INGREDIENTS: Alcohol 70 mL/100 mL
INACTIVE INGREDIENTS: ALOE VERA LEAF; Betaine; GREEN TEA LEAF; CITRIC ACID MONOHYDRATE; CUCUMBER; ISOPROPYL ALCOHOL; Glycerin; Meadowfoamamidopropyl Betaine; Panthenol; PEG-10 DIMETHICONE (600 CST); Water

Kleenex® Reveal™ Moisturizing Foam Hand Sanitizer

Drug Facts

Active ingredient

Ethyl Alcohol 70% v/v

Purpose

Antimicrobial

Uses

For personal hand hygiene to help prevent the spread of bacteria. Kills harmful bacteria or germs.

Warnings

For external use only

Flammability warning

Keep away from open flame and sources of heat.

When using this product avoid contact with eyes. If contact occurs, rinse thoroughly with water.

Stop use and ask a doctor if irritation or redness develops or persists

Keep out of reach of children. If swallowed, get medical help or contact a poison control centre immediately.

Directions

Use enough foam to cover your hands. Supervise children when they use this product. For occasional and personal domestic use. Rub thoroughly into hands for at least 30 seconds. Allow to dry. Use as part of your daily cleansing routine.

Other Information

Report serious side effects from this product to 1-877-561-6587. Do not store above 110 °F (40 °C).

Inactive ingredients

Aloe Barbadensis Leaf Extract, Betaine, Camellia Sensis Leaf Extract, Citric Acid, Cucumis Sativus Fruit Extract (Cucumber), Glycerin, Isopropanol, Meadowfoam Amidopropyl Betaine, Panthenol, PEG-10 Dimethicone, Water/Eau/Aqua

Questions?

1-888-346-4652

Distributed in the U.S. by Kimberly-Clark
Global Sales, LLC, Roswell, GA 30076-2199. Distributed in Canada by Kimberly-Clark Inc.,
Mississauga, Ontario L5B 3Y5

PRINCIPAL DISPLAY PANEL - 532 mL Bottle Label

Kleenex®
BRAND
MARQUE

REVEAL™

MOISTURIZING FOAM HAND SANITIZER

ULTRA

For Personal / Domestic Use Only
18 fl oz (532 mL)